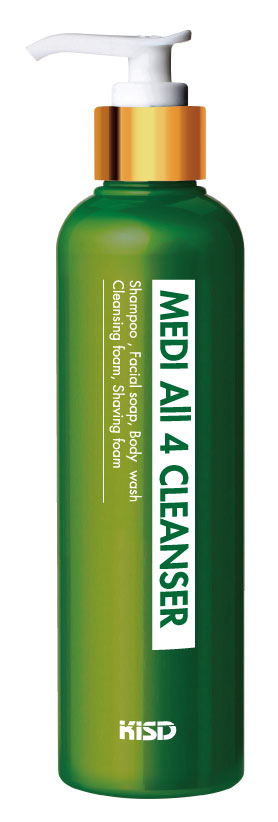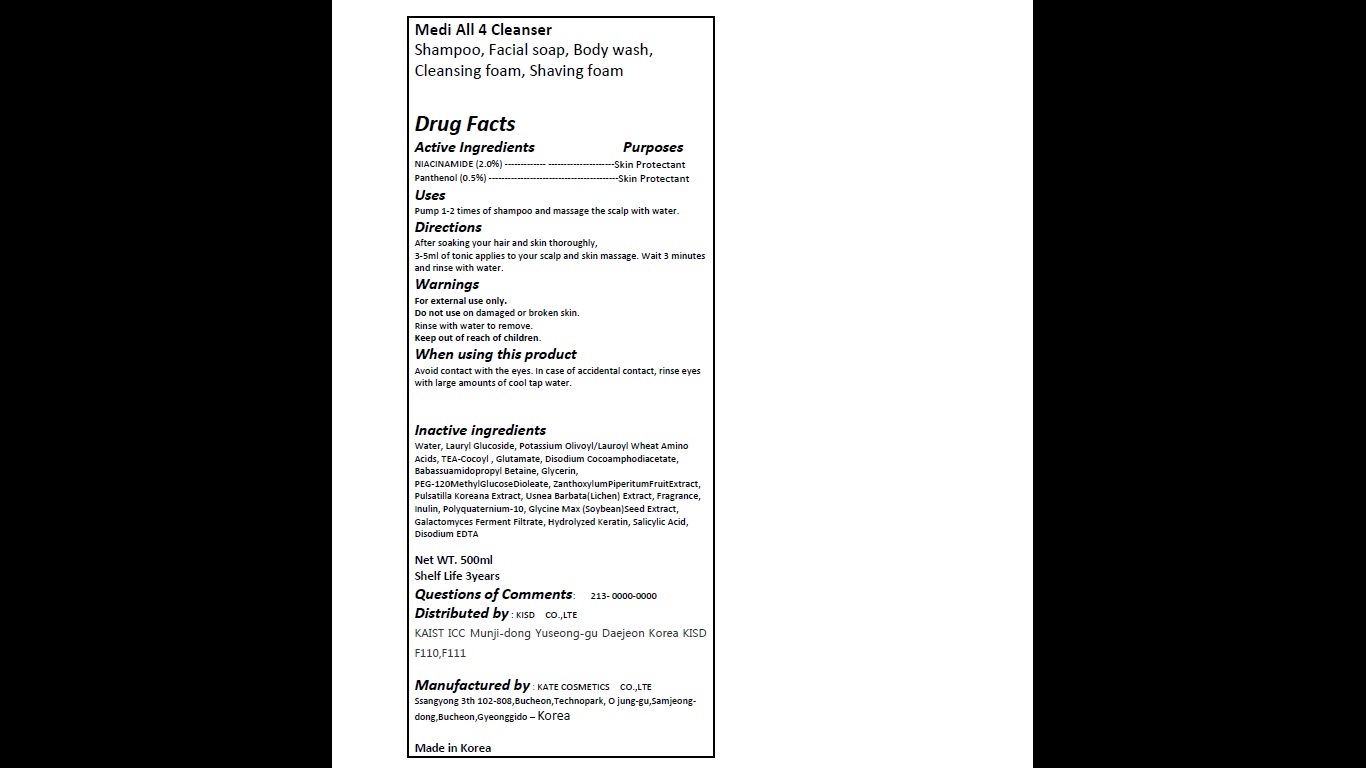 DRUG LABEL: Medi All 4 Cleanser (NIACINAMIDE)
NDC: 70230-1001 | Form: LIQUID
Manufacturer: Katecosmetics. Co., Ltd, (KISD)
Category: otc | Type: HUMAN OTC DRUG LABEL
Date: 20160421

ACTIVE INGREDIENTS: PANTHENOL 0.05 mg/100 mL; NIACINAMIDE 0.2 mg/100 mL
INACTIVE INGREDIENTS: ZANTHOXYLUM PIPERITUM FRUIT PULP; POLYQUATERNIUM-10 (125 MPA.S AT 2%); GLYCINE MAX WHOLE; SALICYLIC ACID; WATER; AMINO ACIDS, WHEAT; LAURYL GLUCOSIDE; POTASSIUM LAUROYL GLUTAMATE; DISODIUM COCOAMPHODIACETATE; GLYCERIN; PEG-120 METHYL GLUCOSE DIOLEATE; PULSATILLA KOREANA ROOT; USNEA BARBATA; INULIN; DISODIUM EDTA-COPPER

Medi All 4 Cleanser

These highlights do not include all the information needed to use. See full prescribing information for Medi All 4 Cleanser. Initial U.S. Approval:2016

Pump 1 to 2 times of shampoo and massage the scalp with water. After soaking your hair and skin thoroughly, 3 to 5 ml of tonic applies to your scalp and skin massage. Wait 3 minutes and rinse with water.

Warnings:
For external use only.
Do not use on damaged or broken skin.
Rinse with water to remove.
Keep out of reach of children.

Inactive ingredients:
Water, Lauryl Glucoside, Potassium Olivoyl/Lauroyl Wheat Amino Acids, TEA-Cocoyl , Glutamate, Disodium Cocoamphodiacetate, Babassuamidopropyl Betaine, Glycerin,
PEG-120MethylGlucoseDioleate, ZanthoxylumPiperitumFruitExtract, Pulsatilla Koreana Extract, Usnea Barbata(Lichen) Extract, Fragrance, Inulin, Polyquaternium-10, Glycine Max (Soybean)Seed Extract, Galactomyces Ferment Filtrate, Hydrolyzed Keratin, Salicylic Acid, Disodium EDTA

INDICATIONS AND USAGE

Avoid contact with the eyes. In case of accidental contact, rinse eyes with large amounts of cool tap water.

PURPOSE

Medi All 4 Cleanser
Shampoo, Facial soap, Body wash, Cleansing foam, Shaving foam, Skin Protectant

Keep out of reach of children.

Active Ingredients Purposes
NIACINAMIDE (2.0%) ------------- ---------------------Skin Protectant
Panthenol (0.5%) -----------------------------------------Skin Protectant

Medi All 4 Cleanser (NIACINAMIDE)

Medi All 4 Cleanser

Shampoo, Facial soap, Body wash, Cleansing foam, Shaving foam

Drug Facts
Active Ingredients Purposes
NIACINAMIDE (2.0%) ------------- ---------------------Skin Protectant
Panthenol (0.5%) -----------------------------------------Skin Protectant
Uses
Pump 1-2 times of shampoo and massage the scalp with water.
Directions
After soaking your hair and skin thoroughly,
3-5ml of tonic applies to your scalp and skin massage. Wait 3 minutes and rinse with water.
Warnings
For external use only.
Do not use on damaged or broken skin.
Rinse with water to remove.
Keep out of reach of children.
When using this product
Avoid contact with the eyes. In case of accidental contact, rinse eyes with large amounts of cool tap water.

Inactive ingredients
Water, Lauryl Glucoside, Potassium Olivoyl/Lauroyl Wheat Amino Acids, TEA-Cocoyl , Glutamate, Disodium Cocoamphodiacetate, Babassuamidopropyl Betaine, Glycerin,
PEG-120MethylGlucoseDioleate, ZanthoxylumPiperitumFruitExtract, Pulsatilla Koreana Extract, Usnea Barbata(Lichen) Extract, Fragrance, Inulin, Polyquaternium-10, Glycine Max (Soybean)Seed Extract, Galactomyces Ferment Filtrate, Hydrolyzed Keratin, Salicylic Acid, Disodium EDTA

Net WT. 500ml
Shelf Life 3years
Questions of Comments: 213- 0000-0000
Distributed by : KISD CO.,LTE
KAIST ICC Munji-dong Yuseong-gu Daejeon Korea KISD F110,F111

Manufactured by : KATE COSMETICS CO.,LTE
Ssangyong 3th 102-808,Bucheon,Technopark, O jung-gu,Samjeong-dong,Bucheon,Gyeonggido – Korea

Made in Korea